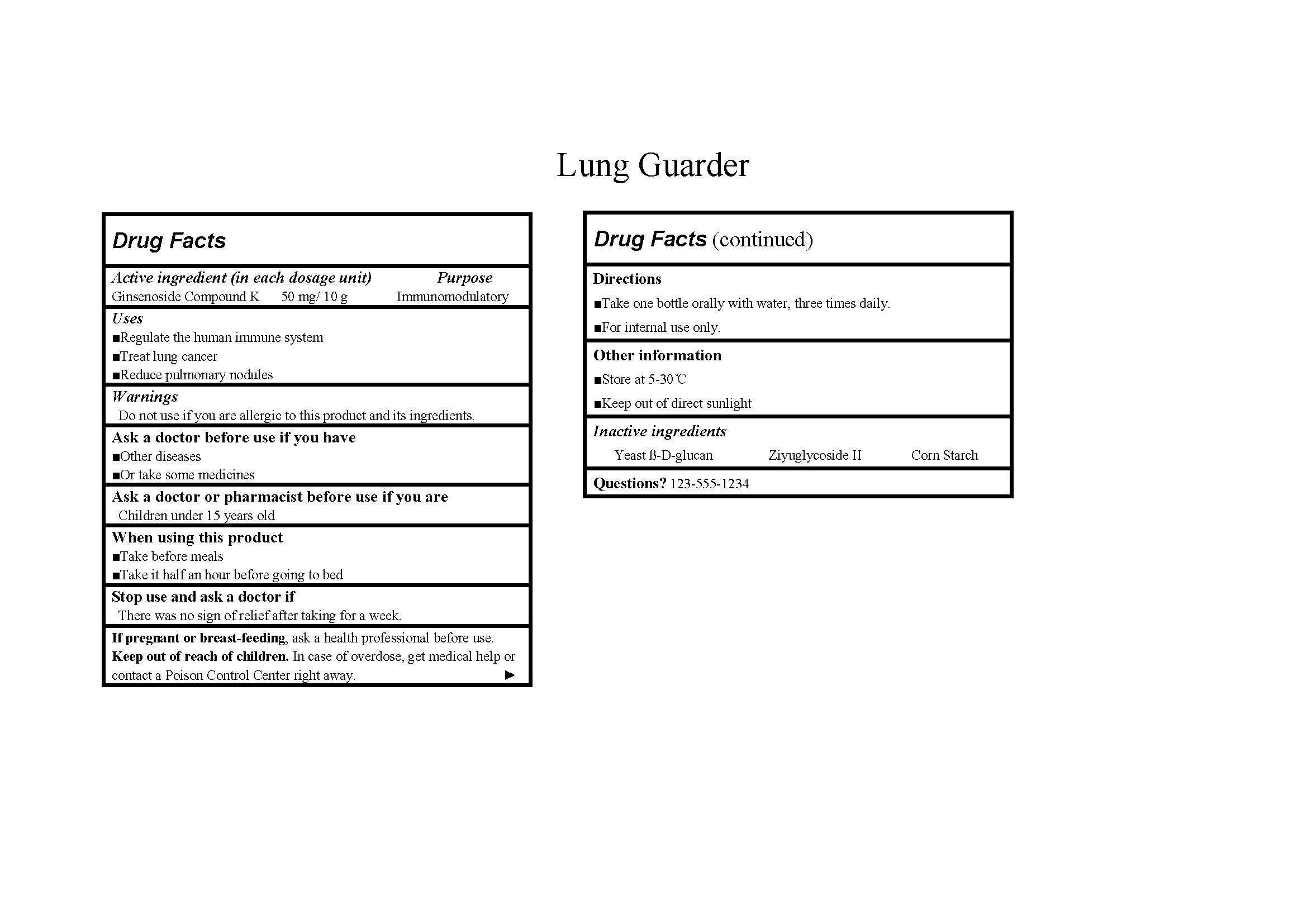 DRUG LABEL: Lung Guarder
NDC: 84428-102 | Form: GRANULE
Manufacturer: Hainan Zehuitang Biotechnology Co., LTD
Category: otc | Type: HUMAN OTC DRUG LABEL
Date: 20240624

ACTIVE INGREDIENTS: GINSENOSIDE COMPOUND K 50 mg/10 g
INACTIVE INGREDIENTS: YEAST .BETA.-D-GLUCAN; STARCH, CORN; ZIYUGLYCOSIDE II

84428-102-01

Active ingredient: Ginsenoside Compound K 50 mg/ 10 g

Purpose: Immunomodulatory

Uses:

Regulate the human immune system,

Treat lung cancer,

Reduce pulmonary nodules

Warnings:

Do not use if you are allergic to this product and its ingredients.

Ask a doctor before use if you have:

Other diseases,

Or take some medicines

Ask a doctor or pharmacist before use if you are Children under 15 years old

When using this product:

Take before meals,

Take it half an hour before going to bed

Stop use and ask a doctor if There was no sign of relief after taking for a week.

PREGNANCY OR BREAST FEEDING

If pregnant or breast-feeding, ask a health professional before use.

Keep out of reach of children. In case of overdose, get medical help or contact a Poison Control Center right away.

Directions:

Take one bottle orally with water, three times daily.

For internal use only.

INACTIVE INGREDIENT

Inactive ingredients: Yeast ß-D-glucan, Ziyuglycoside II, Corn Starch

Questions? 123-555-1234

Other information:

Store at 5-30℃,

Keep out of direct sunlight

Label